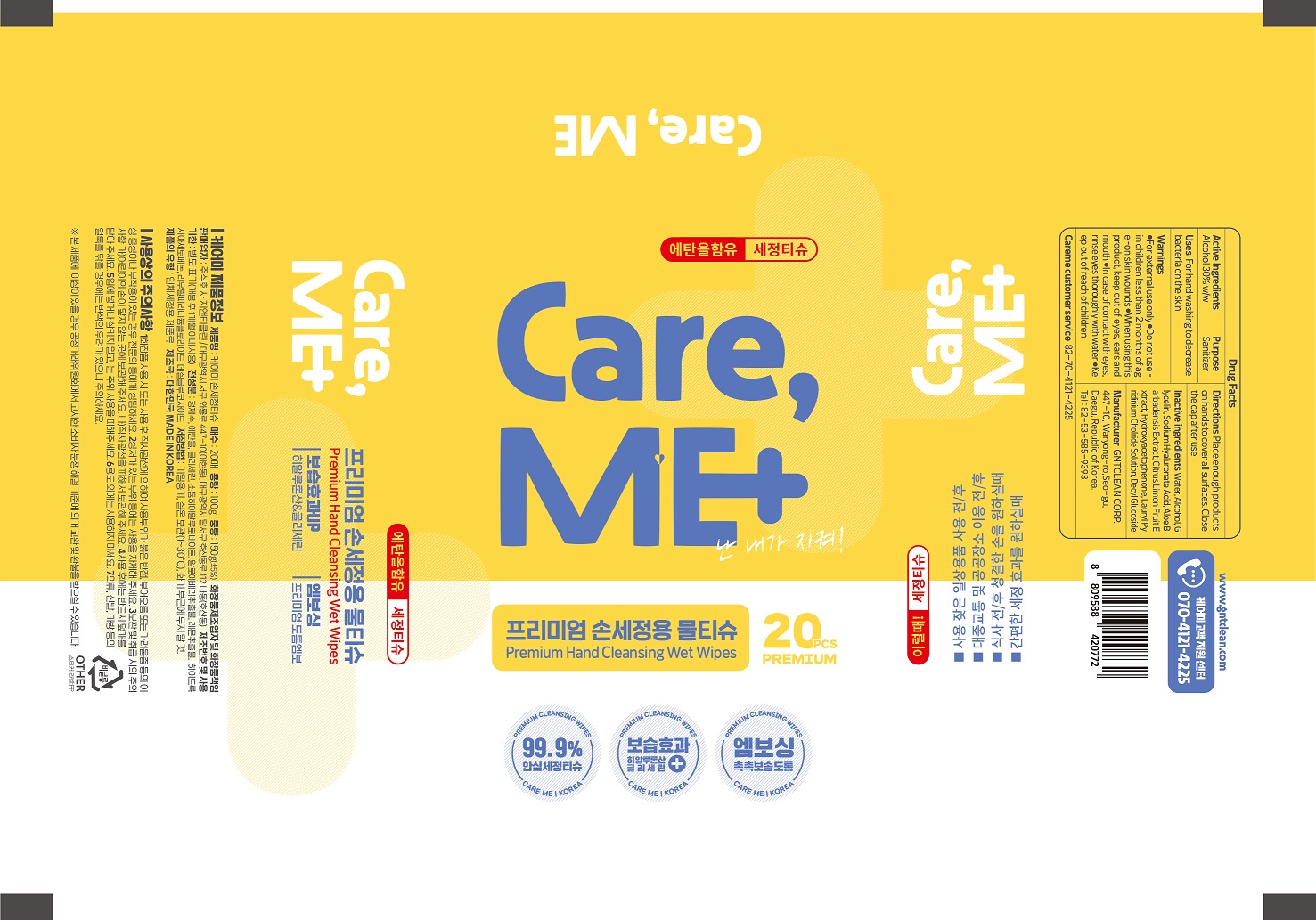 DRUG LABEL: CAREME
NDC: 80351-0001 | Form: LIQUID
Manufacturer: GNTCLEAN CORP
Category: otc | Type: HUMAN OTC DRUG LABEL
Date: 20200829

ACTIVE INGREDIENTS: ALCOHOL 30 g/100 g
INACTIVE INGREDIENTS: GLYCERIN; ALOE VERA LEAF; CITRUS LIMON FRUIT OIL

ACTIVE INGREDIENT

alcohol

INACTIVE INGREDIENT

Water,Glycelin,Sodium Hyaluronate Acid, Aloe Barbadensis Extract,Citrus Limon Fruit Extract, Hydroxyacetophenone,Lauryl Pyridinium Cholride Solution, Dycyl Glucoside

PURPOSE

For hand washing to decrease bacteria on the skin.

keep out of reach of the children

INDICATIONS AND USAGE

Place enough products on hands to cover all surfaces.

Close the cap after use

WARNINGS

For external use only

When using this product

■ If any of the following abnormalities occur, the use of the product shall be suspended

1) In case of red spots, swelling, itching, or irritation during use

2) In case there is an abnormality in the area of application due to direct sunlight

3) The scarred part. Do not use in areas such as eczema or dermatitis.

Consult a dermatologist as symptoms may worsen.

■ Precautions for Storage and Handling

1) Close the cap after use.

2) Keep it out of reach of the baby.

3) Do not store at high or low temperatures or in direct sunlight.

4) Do not use except washing hands.

■ If there is a problem with this product, it can be exchanged or compensated in accordance with the Fair Trade Commission Notice Consumer Dispute Resolution Standards.

DOSAGE AND ADMINISTRATION

for external use only